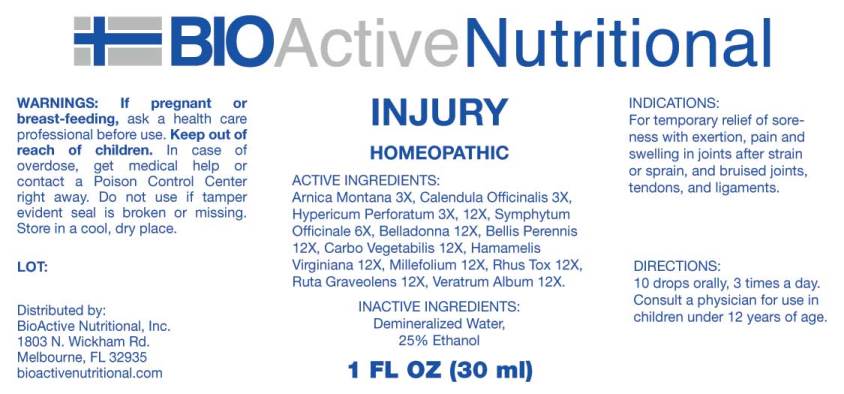 DRUG LABEL: Injury
NDC: 43857-0404 | Form: LIQUID
Manufacturer: BioActive Nutritional, Inc.
Category: homeopathic | Type: HUMAN OTC DRUG LABEL
Date: 20160708

ACTIVE INGREDIENTS: ARNICA MONTANA 3 [hp_X]/1 mL; CALENDULA OFFICINALIS FLOWERING TOP 3 [hp_X]/1 mL; HYPERICUM PERFORATUM 3 [hp_X]/1 mL; COMFREY ROOT 6 [hp_X]/1 mL; ATROPA BELLADONNA WHOLE 12 [hp_X]/1 mL; BELLIS PERENNIS 12 [hp_X]/1 mL; ACTIVATED CHARCOAL 12 [hp_X]/1 mL; HAMAMELIS VIRGINIANA ROOT BARK/STEM BARK 12 [hp_X]/1 mL; ACHILLEA MILLEFOLIUM 12 [hp_X]/1 mL; TOXICODENDRON PUBESCENS LEAF 12 [hp_X]/1 mL; RUTA GRAVEOLENS FLOWERING TOP 12 [hp_X]/1 mL; VERATRUM ALBUM ROOT 12 [hp_X]/1 mL
INACTIVE INGREDIENTS: WATER; ALCOHOL

Drug Facts:

ACTIVE INGREDIENTS:

Arnica Montana 3X, Calendula Officinalis 3X, Hypericum Perforatum 3X, 12X, Symphytum Officinale 6X, Belladonna 12X, Bellis Perennis 12X, Carbo Vegetabilis 12X, Hamamelis Virginiana 12X, Millefolium 12X, Rhus Tox 12X, Ruta Graveolens 12X, Veratrum Album 12X.

INDICATIONS:

For temporary relief of soreness with exertion, pain and swelling in joints after strain or sprain, and bruised joints, tendons, and ligaments.

WARNINGS:

If pregnant or breast-feeding, ask a health care professional before use.

Keep out of reach of children. In case of overdose, get medical help or contact a Poison Control Center right away.

Do not use if tamper evident seal is broken or missing.

Store in cool, dry place.

Keep out of reach of children. In case of overdose, get medical help or contact a Poison Control Center right away.

DIRECTIONS:

10 drops orally, 3 times a day. Consult a physician for use in children under 12 years of age.

INDICATIONS:

For temporary relief of soreness with exertion, pain and swelling in joints after strain or sprain, and bruised joints, tendons, and ligaments.

INACTIVE INGREDIENTS:

Demineralized Water, 25% Ethanol.

QUESTIONS:

Distributed by:

BioActive Nutritional, Inc.

1803 N. Wickham Rd.

Melbourne, FL 32935

bioactivenutritional.com

PACKAGE LABEL DISPLAY:

BIOActive Nutritional

INJURY

HOMEOPATHIC

1 FL OZ (30 ml)